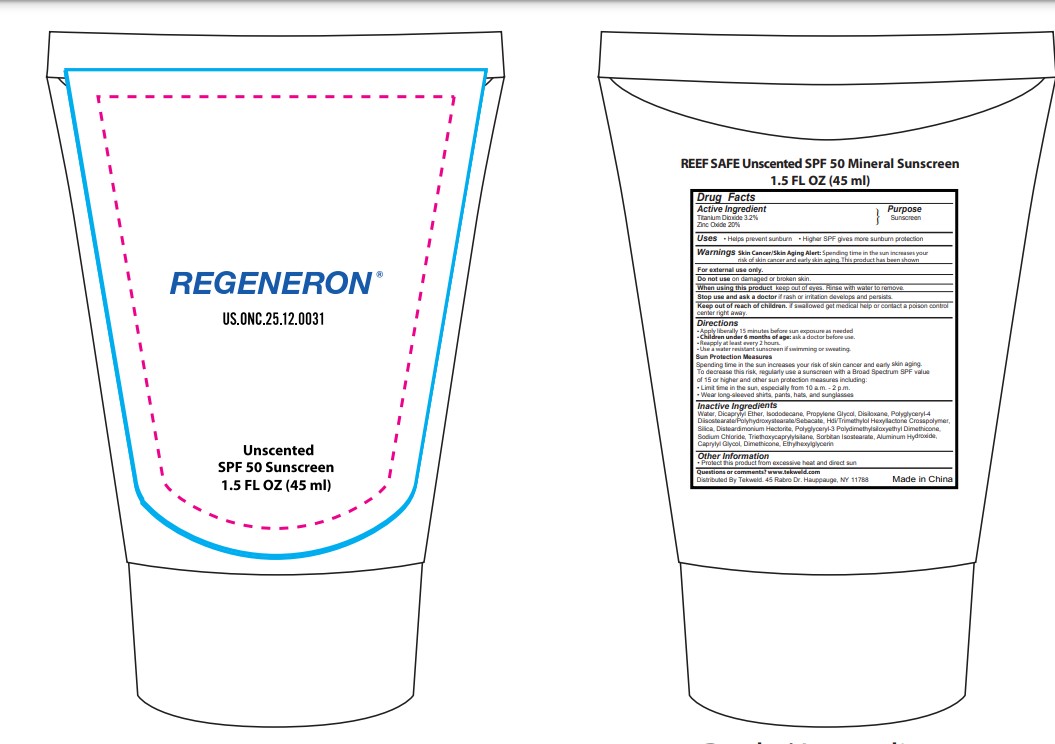 DRUG LABEL: Reef safe unscented SPF 50 mineral sunscreen
NDC: 82953-050 | Form: CREAM
Manufacturer: Cosmuses Cosmetics (Ningbo) Co., Ltd.
Category: otc | Type: HUMAN OTC DRUG LABEL
Date: 20260130

ACTIVE INGREDIENTS: ZINC OXIDE 20 g/100 mL; TITANIUM DIOXIDE 3.2 g/100 mL
INACTIVE INGREDIENTS: ISODODECANE; SILICA; PROPYLENE GLYCOL; DISTEARDIMONIUM HECTORITE; POLYGLYCERYL-3 POLYDIMETHYLSILOXYETHYL DIMETHICONE (4000 MPA.S); DISILOXANE; DIMETHICONE; ETHYLHEXYLGLYCERIN; ALUMINUM HYDROXIDE; TRIETHOXYCAPRYLYLSILANE; SORBITAN ISOSTEARATE; POLYGLYCERYL-4 DIISOSTEARATE/POLYHYDROXYSTEARATE/SEBACATE; SODIUM CHLORIDE; DICAPRYLYL ETHER; HDI/TRIMETHYLOL HEXYLLACTONE CROSSPOLYMER; WATER; CAPRYLYL GLYCOL

Reef safe unscented SPF 50 mineral sunscreen

Drug Facts

Active ingredients

Titanium Dioxide 3.2%

Zinc oxide 20%

Purpose

Sunscreen

Uses

- Helps prevent sunburn
- Higher SPF gives more sunburn protection.

WARNINGS

Skin Cancer/Skin Aging Alert: Spending time in the sun increases your risk of skin cancer and early skin aging.This product has been shown

INDICATIONS AND USAGE

For external use only.

Do not use on damaged or broken skin.

When using this product

Keep out of eyes. Rinse with water to remove.

Stop use and ask a doctor: if rash or irritation develops and persists.

Keep out of reach of children. If swallowed, get medical help or contact a Poison Control Center right away.

Directions

- Apply liberally 15 minutes before sun exposure as needed
- Children under 6 months of age: ask a doctor before use.
- Reapply at least every 2 hours.
- Use a water resistant sunscreen if swimming or sweating

Sun Protection Measures

Spending time in the sun increases your risk of skin cancer and early skin aging.

To decrease this risk, regularly use a sunscreen with a Broad Spectrum SPF value of 15 or higher and other sun protection measures including:

- Limit time in the sun, especially from 10 a.m.-2 p.m.
- Wear long-sleeved shirts, pants, hats, and sunglasses

Inactive ingredients

Water, Dicaprylyl Ether, lsododecane, Propylene Glycol, Disiloxane, Polyglyceryl-4 Diisostearate/Polyhydroxystearate/Sebacate, Hdi/Trimethylol Hexyllactone Crosspolymer, Silica, Disteardimonium Hectorite, Polyglycery-3 Polydimethylsiloxyethyl Dimethicone, Sodium Chloride, Triethoxycaprylylsilane, Sorbitan lsostearate, Aluminum Hydroxide, Caprylyl Glycol, Dimethicone, Ethylhexylglycerin

Other information

- Protect this product from excessive heat and direct sun.

Questions or comments?

www.tekweld.com

Distributed by Tekweld 45 Rabro Dr.Hauppauge, NY 11788